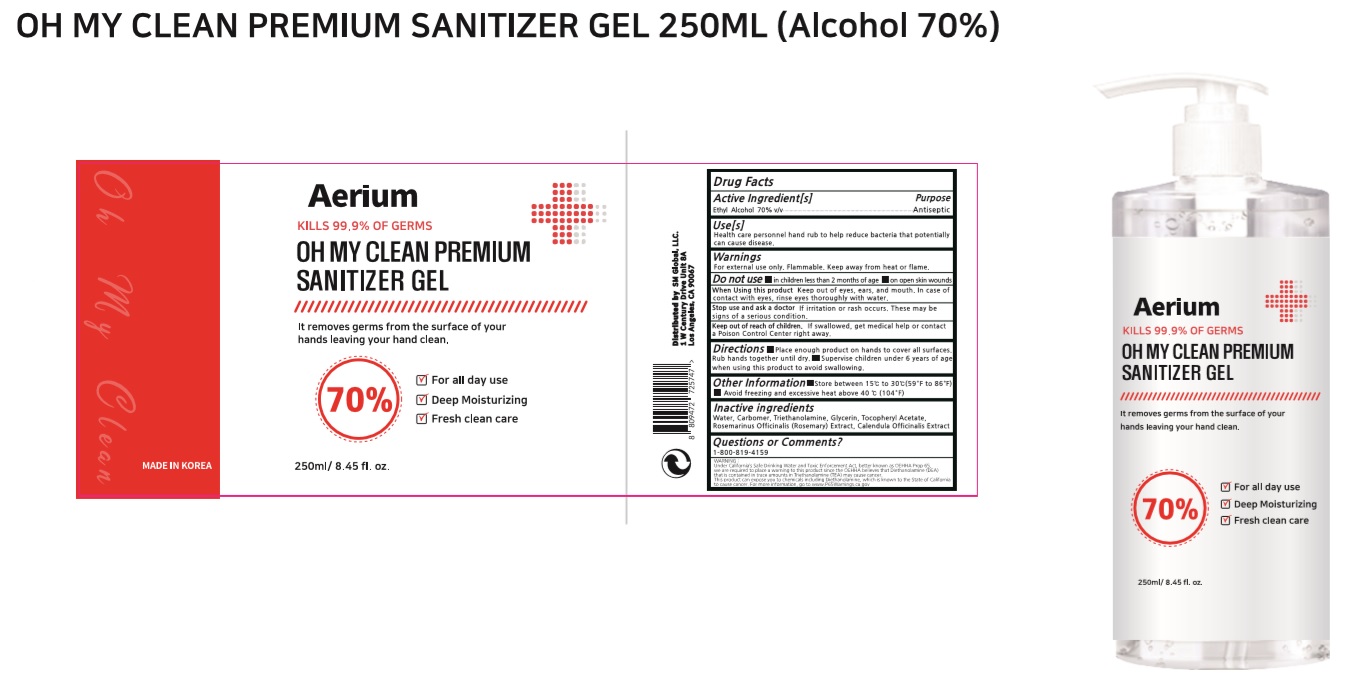 DRUG LABEL: OH MY CLEAN PREMIUM SANITIZER Gel
NDC: 74514-2507 | Form: GEL
Manufacturer: SISKINKOREA CO.,LTD.
Category: otc | Type: HUMAN OTC DRUG LABEL
Date: 20200521

ACTIVE INGREDIENTS: ALCOHOL 175 mL/250 mL
INACTIVE INGREDIENTS: TROLAMINE; GLYCERIN; .ALPHA.-TOCOPHEROL ACETATE; CALENDULA OFFICINALIS WHOLE; WATER; ROSEMARY; CARBOMER HOMOPOLYMER, UNSPECIFIED TYPE

OH MY CLEAN PREMIUM SANITIZER Gel [74514-2507-1]